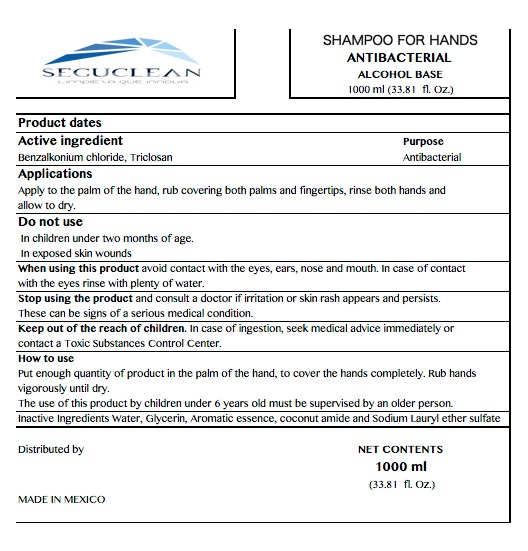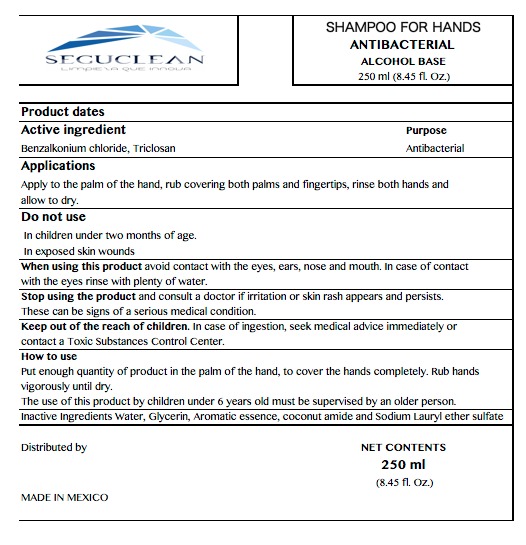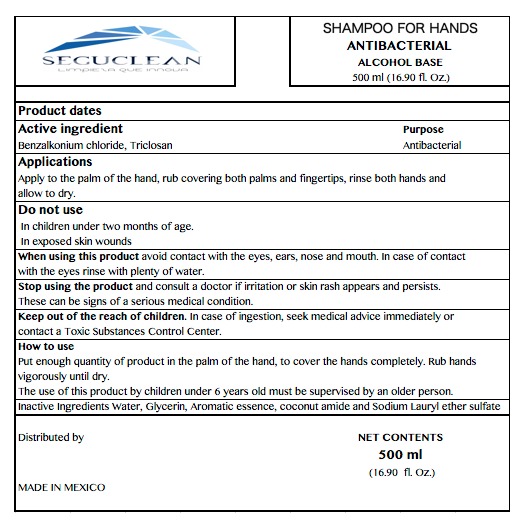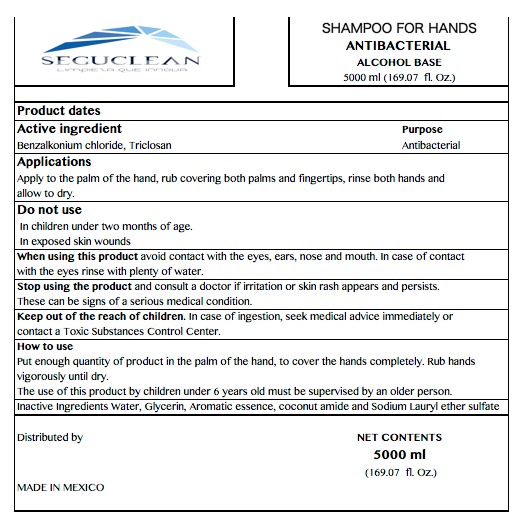 DRUG LABEL: SEGUCLEAN
NDC: 79594-4000 | Form: SHAMPOO
Manufacturer: Productos y Servicios de Limpieza Seguclean S.A. de C.V.
Category: otc | Type: HUMAN OTC DRUG LABEL
Date: 20200721

ACTIVE INGREDIENTS: BENZALKONIUM CHLORIDE 0.001 mg/1 mL
INACTIVE INGREDIENTS: SODIUM CHLORIDE 0.02 mL/1 mL; WATER 0.767 mL/1 mL; TRICLOSAN 0.001 mL/1 mL; ROSE OIL 0.003 mL/1 mL; SODIUM LAURETH-5 SULFATE 0.2 mL/1 mL; DIETHANOLAMINE 0.005 mL/1 mL; GLYCERIN 0.003 mL/1 mL

SANITIZING SHAMPOO

ACTIVE INGREDIENT

BENZALKONIUM CHLORIDE, TRICLOSAN

INACTIVE INGREDIENTS

WATER, GLYCERYN, AROMATIC ESSENCE, COCONUT AMIDE AND SODIUM LAURYL ETHER SULFATE

INDICATIONS AND USAGE

APPLY TO THE PALM OF THE HAND, RUB COVERING BOTH PALMS AND FINGERTIPS, RINSE BOTH HANDS AND ALLOW TO DRY.

DO NOT USE IN CHILDREN UNDER TWO MONTHS OF AGE.

DON NOT USE IN EXPOSED WOUNDS

STOP USE

STOP USING THE PRODUCT AND CONSULT A DOCTOR IF IRRITATION OR SKIN RASH APPEARS AND PERSISTS.
THESE CAN BE SIGNS OF A SERIOUS MEDICAL CONDITION.

PURPOSE

PURPOSE ANTIBACTERIAL

KEEP OUT OF THE REACH OF CHILDREN. IN CASE OF INGESTION, SEEK MEDICAL ADVICE IMMEDIATELY OR CONTACT A TOXIC SUBSTANCES CONTROL CENTER.

WARNINGS AND PRECAUTIONS

THE USE OF THIS PRODUCT IN BY CHILDREN UNDER 6 YEARS OLD MUST BE SUPERVISED BY AND OLDER PERSON.

WARNINGS

KEEP OUR OF THE REACH OF CHILDREN

DOSAGE AND ADMINISTRATION

APPLY TO THE PALM OF THE HAND, RUB COVERING BOTH HANDS AND FINGERTIPS, RINSE BOTH HANDS AND ALLOW TO DRY.